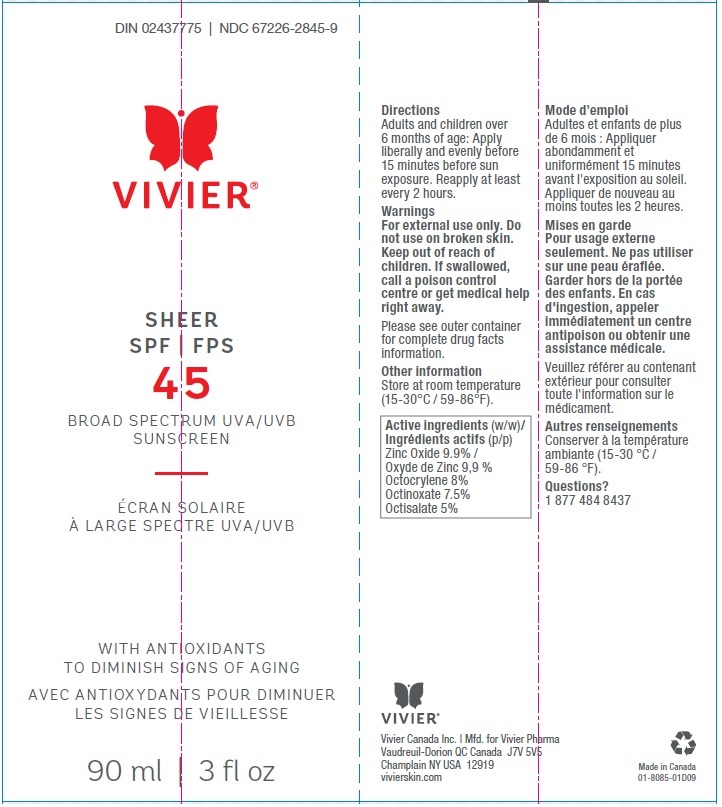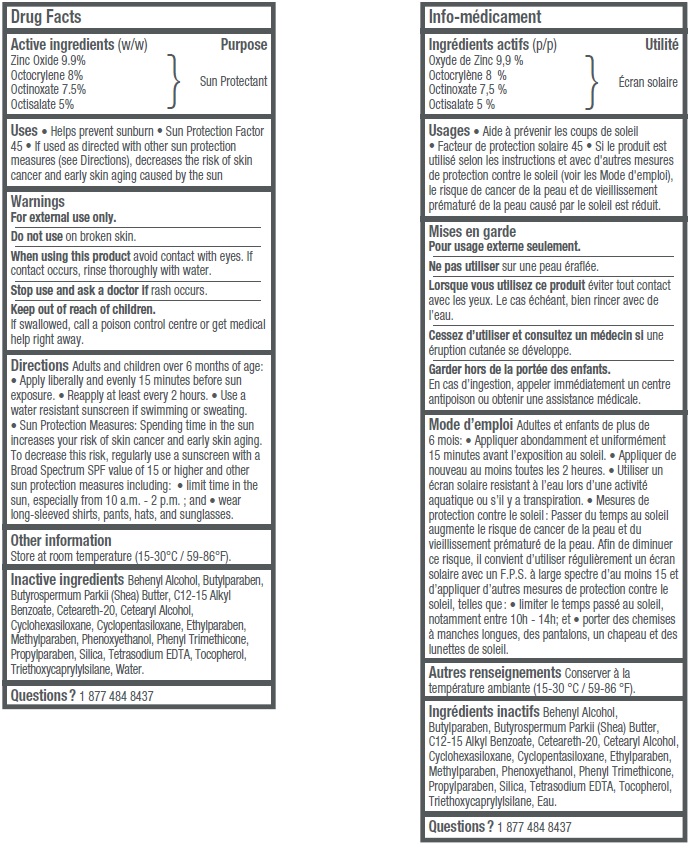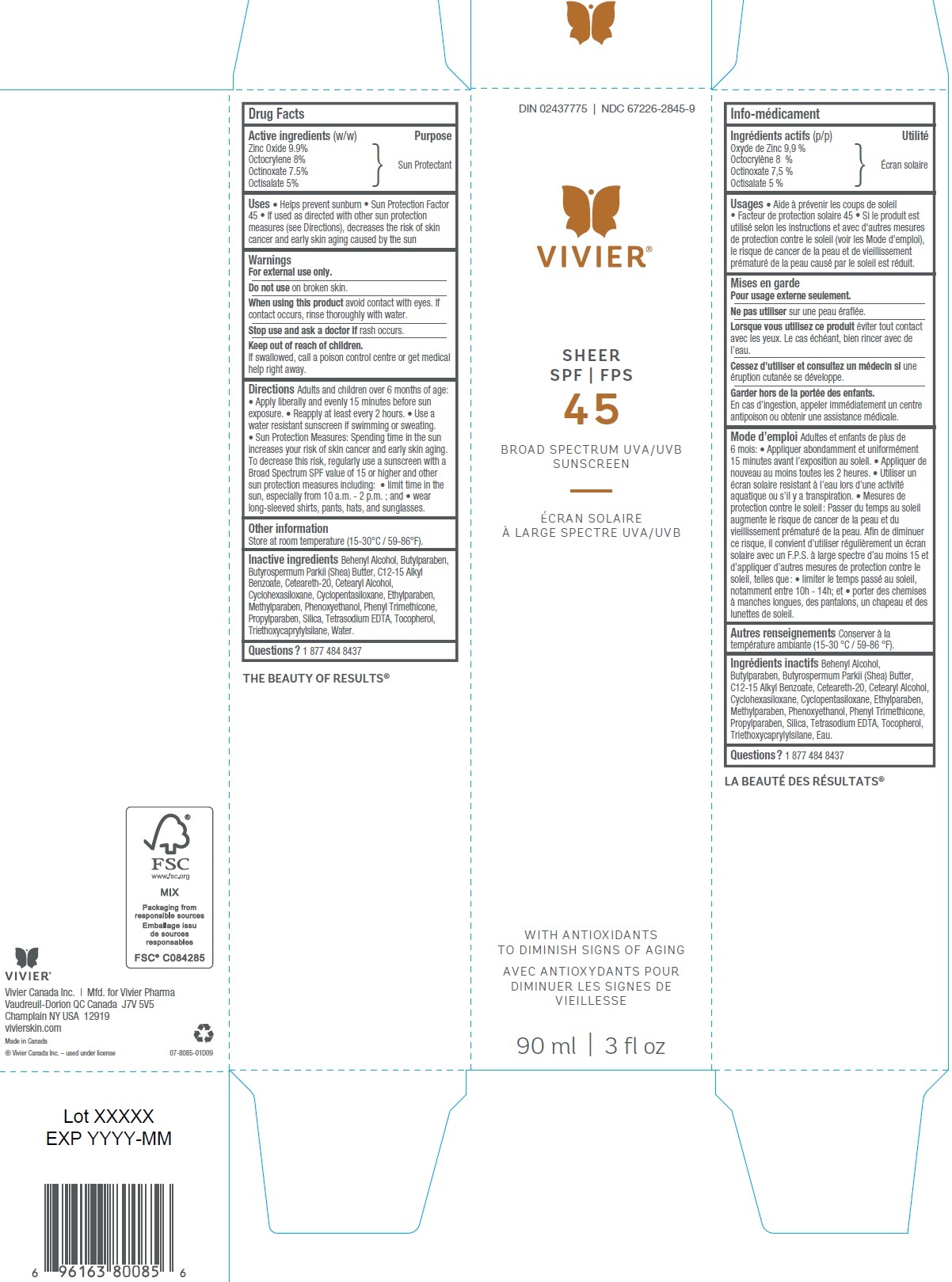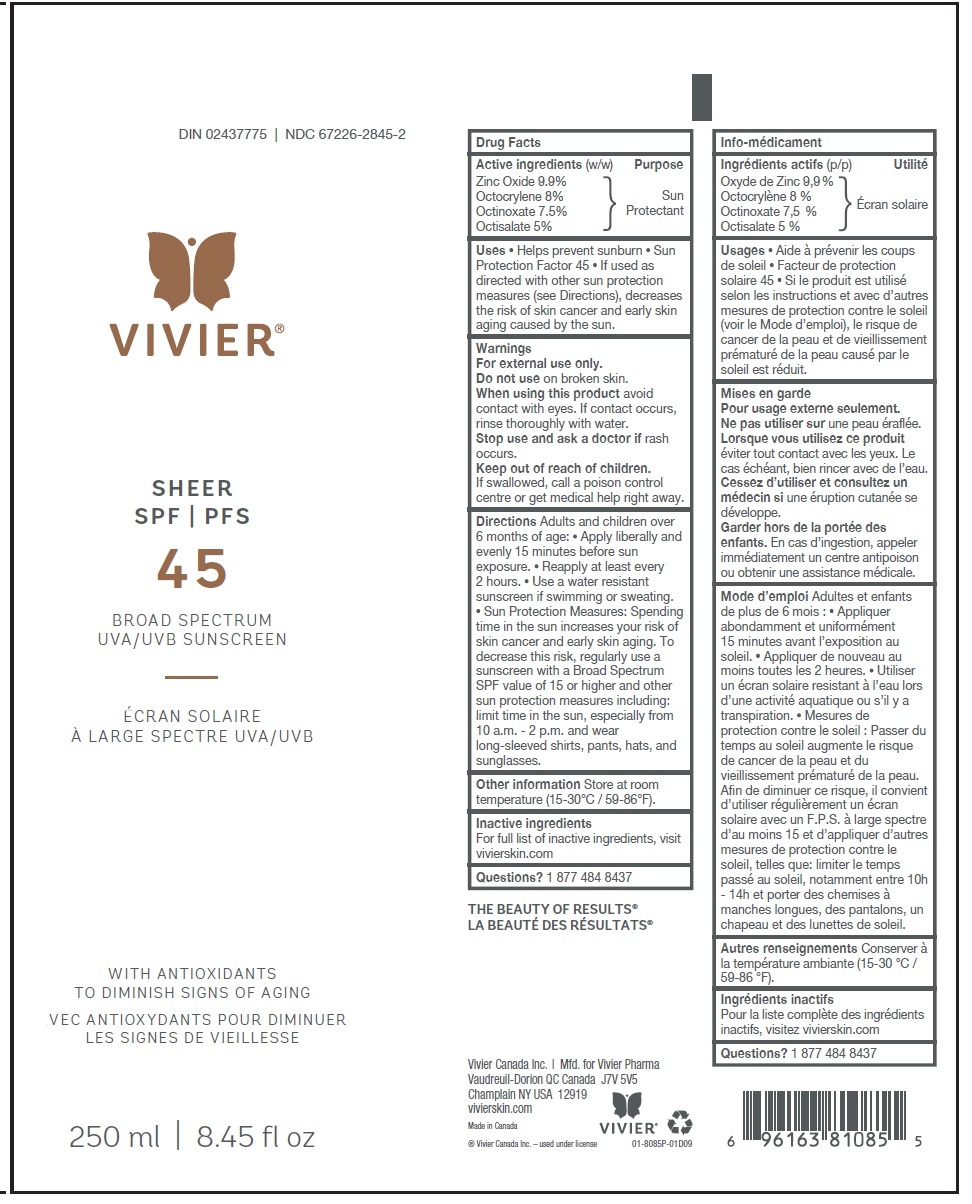 DRUG LABEL: Vivier Sheer SPF 45
NDC: 67226-2852 | Form: LOTION
Manufacturer: Vivier Pharma, Inc.
Category: otc | Type: HUMAN OTC DRUG LABEL
Date: 20231027

ACTIVE INGREDIENTS: ZINC OXIDE 99 mg/1 mL; OCTOCRYLENE 80 mg/1 mL; OCTINOXATE 75 mg/1 mL; OCTISALATE 50 mg/1 mL
INACTIVE INGREDIENTS: DOCOSANOL; BUTYLPARABEN; SHEA BUTTER; ALKYL (C12-15) BENZOATE; POLYOXYL 20 CETOSTEARYL ETHER; CETOSTEARYL ALCOHOL; CYCLOMETHICONE 6; CYCLOMETHICONE 5; ETHYLPARABEN; METHYLPARABEN; PHENOXYETHANOL; PHENYL TRIMETHICONE; PROPYLPARABEN; SILICON DIOXIDE; EDETATE SODIUM; TOCOPHEROL; TRIETHOXYCAPRYLYLSILANE; WATER

Vivier Sheer SPF 45

Active ingredients (w/w)

Zinc Oxide 9.9% Octocrylene 8% Octinoxate 7.5% Octisalate 5%

Purpose

Sun Protectant

Uses

• Helps prevent sunburn • Sun Protection Factor 45 • If used as directed with other sun protection measures (see Directions), decreases the risk of skin cancer and early skin aging caused by the sun

Warnings

For external use only.

Do not use

on broken skin.

When using this product

avoid contact with eyes. If contact occurs, rinse thoroughly with water.

Stop use and ask a doctor if

rash occurs.

Keep out of reach of children.

If swallowed, call a poison control centre or get medical help right away.

Directions

Adults and children over 6 months of age: • Apply liberally and evenly 15 minutes before sun exposure • Reapply at least every 2 hours • Use a water resistant sunscreen if swimming or sweating. • Sun Protection Measures: Spending time in the sun increases your risk of skin cancer and early skin aging. To decrease this risk, regularly use a sunscreen with a Broad Spectrum SPF value of 15 or higher and other sun protection measures including: • limit time in the sun, especially from 10 a.m.– 2 p.m.; and • wear long-sleeved shirts, pants, hats, and sunglasses.

Other information

Store at room temperature (15-30°C / 59-86°F).

Inactive ingredients

Behenyl Alcohol, Butylparaben, Butyrospermum Parkii (Shea) Butter, C12-15 Alkyl Benzoate, Ceteareth-20, Cetearyl Alcohol, Cyclohexasiloxane, Cyclopentasiloxane, Ethylparaben, Methylparaben, Phenoxyethanol, Phenyl Trimethicone, Propylparaben, Silica, Tetrasodium EDTA, Tocopherol, Triethoxycaprylylsilane, Water.

Questions?

1 877 484 8437